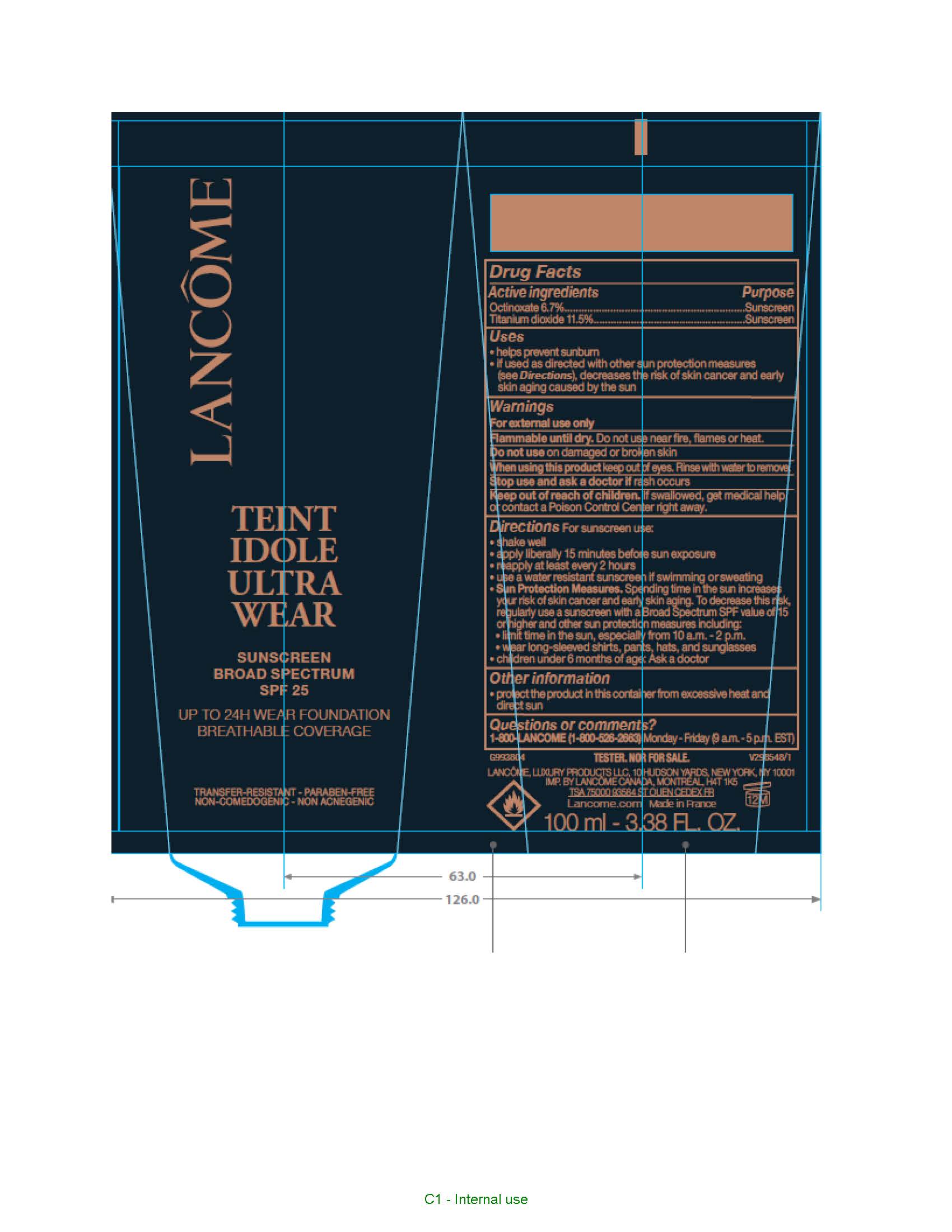 DRUG LABEL: Lancome Paris Teint Idole Ultra Wear Breathable Coverage Foundation Reno Broad Spectrum SPF 25 Sunscreen
NDC: 51150-303 | Form: LIQUID
Manufacturer: SICOS ET CIE
Category: otc | Type: HUMAN OTC DRUG LABEL
Date: 20240626

ACTIVE INGREDIENTS: OCTINOXATE 67 mg/1 mL; TITANIUM DIOXIDE 115 mg/1 mL
INACTIVE INGREDIENTS: WATER; DIMETHICONE; ISODODECANE; ALCOHOL; TRIMETHYLSILOXYSILICATE (M/Q 0.6-0.8); BUTYLENE GLYCOL; PEG-10 DIMETHICONE (600 CST); PERLITE; MAGNESIUM POTASSIUM ALUMINOSILICATE FLUORIDE; MORINGA OLEIFERA SEED; SMALLANTHUS SONCHIFOLIUS ROOT JUICE; CALCIUM ALUMINUM BOROSILICATE; GLYCERIN; DIPENTAERYTHRITYL TETRAHYDROXYSTEARATE/TETRAISOSTEARATE; .ALPHA.-GLUCAN OLIGOSACCHARIDE; HYALURONATE SODIUM; SILICON DIOXIDE; HEXAMETHYLENE DIISOCYANATE/TRIMETHYLOL HEXYLLACTONE CROSSPOLYMER; POWDERED CELLULOSE; ALUMINUM HYDROXIDE; MAGNESIUM SULFATE, UNSPECIFIED FORM; NYLON-12; SODIUM PHOSPHATE, DIBASIC, ANHYDROUS; DISODIUM STEAROYL GLUTAMATE; ISOPROPYL LAUROYL SARCOSINATE; HYDROGEN DIMETHICONE (13 CST); CITRIC ACID MONOHYDRATE; DIISOPROPYL SEBACATE; BIS-PEG/PPG-14/14 DIMETHICONE; EMMENTAL LACTOBACILLUS; MALTODEXTRIN; DISTEARDIMONIUM HECTORITE; BUTYLATED HYDROXYTOLUENE; TOCOPHEROL; PHENOXYETHANOL; FERRIC OXIDE RED

Drug Facts

Active ingredients

Octinoxate 6.7%

Titanium dioxide 11.5%

Purpose

Sunscreen

Uses

- helps prevent sunburn
- if used as directed with other sun protection measures (see Directions), decreases the risk of skin cancer and early skin aging caused by the sun

Warnings

For external use only

Flammable until dry.

Do not use near fire, flame, or heat.

Do not use

on damaged or broken skin

When using this product

keep out of eyes. Rinse with wate to remove.

Stop use and ask a doctor if

rash occurs

Keep out of reach of children.

If swallowed, get medical help or contact a Poison Control Center right away.

Directions

For sunscreen use:

● shake well

● apply liberally 15 minutes before sun exposure

● reapply at least every 2 hours

● use a water resistant sunscreen if swimming or sweating

● Sun Protection Measures. Spending time in the sun increases your risk of skin cancer and early skin aging. To decrease this risk, regularly use a sunscreen with a Broad Spectrum SPF value of 15 or higher and other sun protection measures including:

● limit time in the sun, especially from 10 a.m. – 2 p.m.

● wear long-sleeved shirts, pants, hats, and sunglasses

● children under 6 months of age: Ask a doctor

Other information

protect the product in this container from excessive heat and direct sun

Inactive ingredients

water, dimethicone, isododecane, alcohol denat., trimethylsiloxysilicate, butylene glycol, PEG-10 dimethicone, perlite, synthetic fluorphlogopite, moringa oleifera seed extract, polymnia sonchifolia root juice, calcium aluminum borosilicate, glycerin, dipentaerythrityl tetrahydroxystearate/tetraisostearate, alpha-glucan oligosaccharide, sodium hyaluronate, silica, silica silylate, HDI/trimethylol hexyllactone crosspolymer, cellulose, aluminum hydroxide, magnesium sulfate, nylon-12, disodium phosphate, disodium stearoyl glutamate, isopropyl lauroyl sarcosinate, hydrogen dimethicone, citric acid, diisopropyl sebacate, bis-PEG/PPG-14/14 dimethicone, lactobacillus, maltodextrin, disteardimonium hectorite, BHT, tocopherol, phenoxyethanol; may contain: titanium dioxide, iron oxides, chromium oxide greens

Questions or comments?

1-800-LANCOME

(1-800-526-2663)

Monday - Friday

(9 a.m. - 5 p.m. EST)